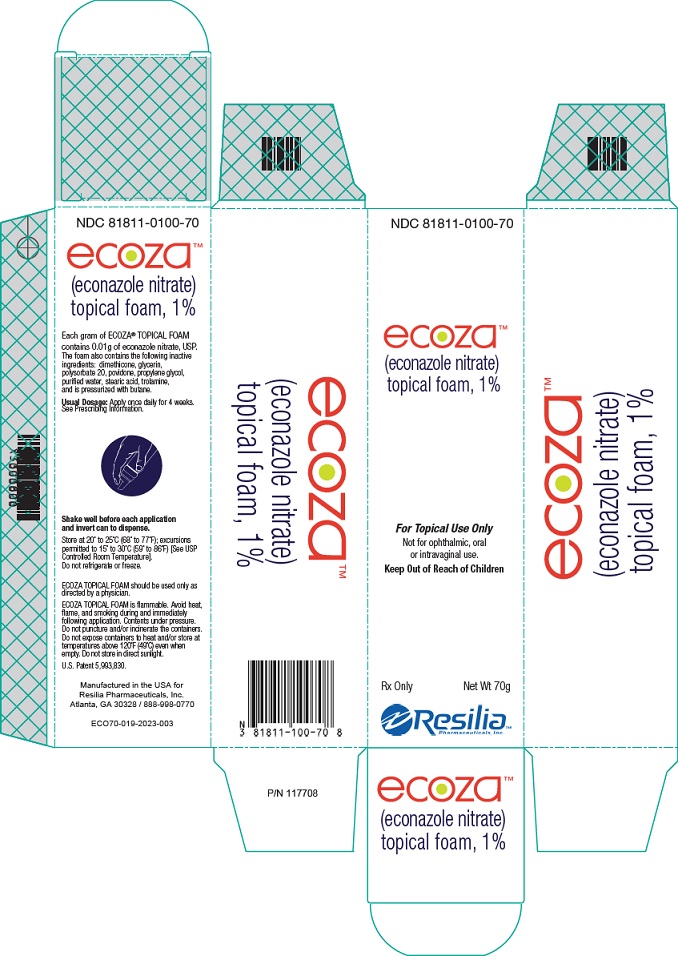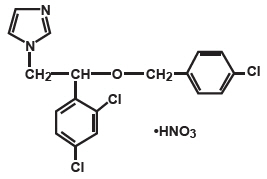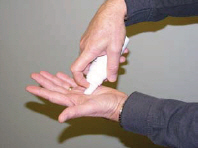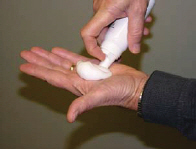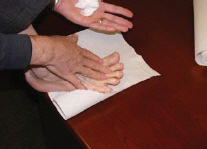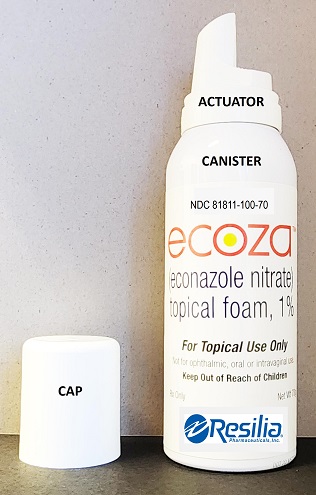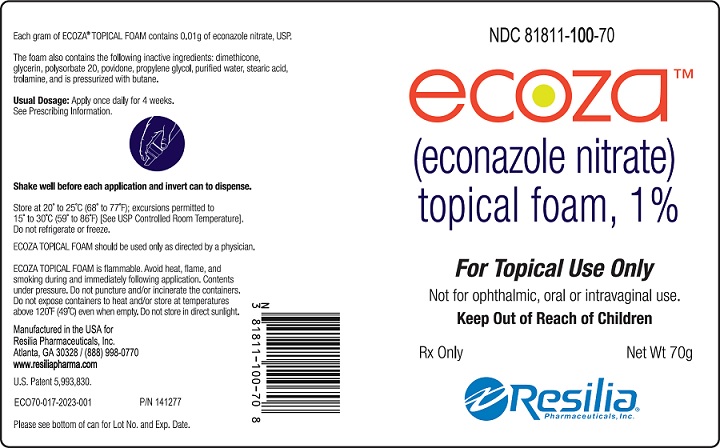 DRUG LABEL: Ecoza
NDC: 81811-100 | Form: AEROSOL, FOAM
Manufacturer: Resilia Pharmaceuticals, Inc.
Category: prescription | Type: HUMAN PRESCRIPTION DRUG LABEL
Date: 20231204

ACTIVE INGREDIENTS: ECONAZOLE NITRATE 10 mg/1 g
INACTIVE INGREDIENTS: DIMETHICONE; GLYCERIN; POLYSORBATE 20; POVIDONE K30; PROPYLENE GLYCOL; STEARIC ACID; TROLAMINE; WATER; BUTANE

HIGHLIGHTS OF PRESCRIBING INFORMATION

These highlights do not include all the information needed to use ECOZA safely and effectively. See full prescribing information for ECOZA.
ECOZA®(econazole nitrate) topical foam, 1%, for topical use
Initial U.S. Approval: 1982

1 INDICATIONS AND USAGE

Ecoza is an azole antifungal indicated for the treatment of interdigital tinea pedis caused by Trichophyton rubrum, Trichophyton mentagrophytes, and Epidermophyton floccosumin patients 12 years of age and older. (1)

2 DOSAGE AND ADMINISTRATION

- For topical use only; not for oral, ophthalmic, or intravaginal use. (2)
- Apply once daily for 4 weeks. (2)

3 DOSAGE FORMS AND STRENGTHS

Foam, 1%. (3)

4 CONTRAINDICATIONS

None. (4)

5 WARNINGS AND PRECAUTIONS

Contents are flammable. Instruct the patient to avoid heat, flame, and/or smoking during and immediately following application. (5.1)

6 ADVERSE REACTIONS

During clinical trials with Ecoza topical foam, the most common adverse reactions were application site reactions which occurred in less than 1% of subjects in both the Ecoza and vehicle arms. (6.1)

To report SUSPECTED ADVERSE REACTIONS, contact Resilia Pharmaceuticals at 1-888-998-0770 or FDA at 1-800-FDA-1088 or www.fda.gov/medwatch.

FULL PRESCRIBING INFORMATION

1 INDICATIONS AND USAGE

Ecoza (econazole nitrate) topical foam, 1%, is indicated for the treatment of interdigital tinea pedis caused by Trichophyton rubrum, Trichophyton mentagrophytes,and Epidermophyton floccosumin patients 12 years of age and older.

2 DOSAGE AND ADMINISTRATION

Ecoza topical foam, 1% is for topical use only. Ecoza topical foam, 1% is not for oral, ophthalmic, or intravaginal use.

Ecoza topical foam, 1% should be applied to cover affected areas once daily for 4 weeks.

3 DOSAGE FORMS AND STRENGTHS

Foam, 1%. Each gram of Ecoza topical foam, 1%, contains 10 mg of econazole nitrate in a white to off-white foam.

4 CONTRAINDICATIONS

None.

5 WARNINGS AND PRECAUTIONS

5.1 Flammability

Ecoza topical foam is flammable. Avoid heat, flame, and smoking during and immediately following application. Contents under pressure. Do not puncture and/or incinerate the containers. Do not expose containers to heat and/or store at temperatures above 120°F (49°C) even when empty. Do not store in direct sunlight.

6 ADVERSE REACTIONS

6.1 Clinical Trials Experience

Because clinical trials are conducted under widely varying conditions, adverse reaction rates observed in the clinical trials of a drug cannot be directly compared to rates in the clinical trials of another drug and may not reflect the rates observed in practice.

In two double-blind, vehicle-controlled clinical trials, 495 subjects were exposed to Ecoza topical foam or vehicle (246 subjects were exposed to Ecoza topical foam, 1% and 249 were exposed to vehicle). Subjects with interdigital tinea pedis applied foam or vehicle once daily for approximately 28 days. During clinical trials with Ecoza topical foam, the most common adverse reactions were application site reactions which occurred in less than 1% of subjects in both the Ecoza and vehicle arms.

7 DRUG INTERACTIONS

7.1 Warfarin

Concomitant administration of econazole and warfarin has resulted in enhancement of anticoagulant effect. Most cases reported product application with use under occlusion, genital application, or application to a large body surface area which may increase the systemic absorption of econazole nitrate. Monitoring of International Normalized Ratio (INR) and/or prothrombin time may be indicated especially for patients who apply econazole to large body surface areas, in the genital area, or under occlusion.

8 USE IN SPECIFIC POPULATIONS

8.1 Pregnancy

TERATOGENIC EFFECTS

Pregnancy Category C

There are no adequate and well-controlled trials with Ecoza topical foam in pregnant women. Ecoza topical foam should be used during pregnancy only if the potential benefit justifies the potential risk to the fetus.

Econazole nitrate has not been shown to be teratogenic when administered orally to mice, rabbits or rats. Fetotoxic or embryotoxic effects were observed in Segment I oral studies with rats receiving 10 to 40 times the human dermal dose. Similar effects were observed in Segment II or Segment III studies with mice, rabbits and/or rats receiving oral doses 80 or 40 times the human dermal dose.

8.3 Nursing Mothers

It is not known whether econazole nitrate is excreted in human milk. Because many drugs are excreted in human milk, caution should be exercised when econazole nitrate is administered to a nursing woman. Following oral administration of econazole nitrate to lactating rats, econazole and/or metabolites were excreted in milk and were found in nursing pups.

8.4 Pediatric Use

Of the 173 subjects treated with Ecoza topical foam, 1% in the clinical trials, 2 subjects were 12 to 17 years old. In a pediatric maximal use trial, Ecoza topical foam, 1% was applied once daily to eighteen subjects aged 12 to 17 years with interdigital tinea pedis for 28 days [ see Clinical Pharmacology (12.3)]. The safety findings for subjects 12 to 17 years were similar to those in adult population.

8.5 Geriatric Use

Of the 173 subjects treated with Ecoza topical foam, 1% in the adult clinical trials, 6 subjects were 65 years or older. No overall differences in safety or effectiveness were observed between these subjects and younger subjects.

11 DESCRIPTION

Ecoza (econazole nitrate) topical foam, 1% contains the azole antifungal agent, econazole nitrate in an oil-in-water emulsion base consisting of the following inactive ingredients: dimethicone, glycerin, polysorbate 20, povidone, propylene glycol, stearic acid, trolamine, purified water and butane as a propellant. Each gram of Ecoza topical foam, 1% contains 10 mg of econazole nitrate, USP, in a white to off-white foam. Ecoza topical foam, 1% is alcohol (ethanol)-free and for topical use only.

Chemically, econazole nitrate is 1-[2-{(4-chloro-phenyl)methoxy}-2-(2,4-dichlorophenyl) ethyl]-1H-imidazole mononitrate. Econazole nitrate has the molecular formula C18H15Cl3N2O. HNO3 and a molecular weight of 444.70. Its molecular structure is as follows:

12 CLINICAL PHARMACOLOGY

12.1 Mechanism of Action

Ecoza topical foam is an azole antifungal [ see Clinical Pharmacology (12.4)] .

12.2 Pharmacodynamics

The pharmacodynamics of Ecoza topical foam, 1% have not been established .

12.3 Pharmacokinetics

The systemic absorption of Ecoza topical foam, 1% following topical application was studied in one clinical trial in adults and one clinical study in pediatric subjects.

In the adult trial, 19 subjects (male and female) with tinea pedis applied Ecoza topical foam, 1% once daily for 29 days. Subjects applied a mean daily amount of 2.4 g of Ecoza topical foam, 1% to soles, toes, interdigital spaces and tops of both feet up to the ankles. Blood samples were obtained on Day 29 at pre-dose and 1, 2, 4, 6, 8, and 12 hours after application. Results (mean ± SD) showed the time to reach peak plasma concentrations (Tmax) was 6.8 ± 5.1 h with maximum concentration (Cmax) of 417 ± 218 pg/ml. The area under the concentration time curve for the first 12 hours post application on Day 29 (AUC(0-12)) was 3440 ± 1920 pg-h/ml.

In the pediatric trial, 18 subjects (male and female ages 12 - 17) with interdigital tinea pedis and positive fungal cultures were treated with Ecoza topical foam, 1% once daily for 4 weeks. Subjects applied a mean daily amount of 3.2 g of Ecoza topical foam, 1% to soles, toes, interdigital spaces and tops of both feet up to the ankles. Blood samples were obtained on Day 28 at pre-dose and 7 h and 11 h post-dose. The mean ± SD econazole plasma concentration was 397 ± 289, 534 ± 745 and 575 ± 638 pg/mL at pre-dose and 7 h and 11 h post-dose, respectively.

12.4 Microbiology

Mechanism of Action

Econazole nitrate, an azole antifungal agent, inhibits fungal cytochrome P-450-mediated 14 alpha-lanosterol demethylase enzyme. This enzyme functions to convert lanosterol to ergosterol. The accumulation of 14 alpha-methyl sterols correlates with the subsequent loss of ergosterol in the fungal cell wall and may be responsible for the fungistatic activity of econazole. Mammalian cell demethylation is less sensitive to econazole inhibition.

Activity in vitro and in clinical infections

Econazole nitrate has been shown to be active against most strains of the following microorganisms, both in vitro and in clinical infections [ see Indications and Usage (1)].

Trichophyton rubrum

Epidermophyton floccosum

Trichophyton mentagrophytes

13 NONCLINICAL TOXICOLOGY

13.1 Carcinogenesis, Mutagenesis, Impairment of Fertility

Long-term animal studies to determine the carcinogenic potential of Ecoza topical foam have not been performed.

Oral administration of econazole nitrate in rats has been reported to produce prolonged gestation.

14 CLINICAL STUDIES

In two multi-center, randomized, double-blind, vehicle-controlled clinical trials a total of 505 subjects with interdigital tinea pedis were randomized 1:1 to Ecoza topical foam or vehicle; subjects applied the assigned medication once daily for 4 weeks. The severity of erythema, scaling, fissuring, maceration, vesiculation, and pruritus were graded using a 4-point scale (none, mild, moderate, severe). Subjects had KOH examination and fungal cultures taken to confirm eligibility. A total of 339 subjects with positive fungal cultures were evaluated for efficacy. Efficacy was evaluated on Day 43, 2 weeks post-treatment with treatment success being defined as complete cure (negative KOH and fungal culture and no evidence of clinical disease). The study population ranged in age from 12 to 71 years with 5 subjects less than 18 years of age at baseline. The subjects were 71% male and 51% Caucasian. Table 1 presents the efficacy results for each trial.

Table 1: Efficacy Results at Two Weeks Post-treatment (Day 43)
Complete Cure, Effective Treatment and Mycological Cure
 | Trial 1 |  | Trial 2
 | Ecoza topical foam 1%; N = 82; n(%) | Foam Vehicle; N = 83; n(%) | Ecoza topical foam, 1%; N = 91; n(%) | Foam Vehicle; N = 83; n(%)
Complete curea | 19 (23.2%) | 2 (2.4%) | 23 (25.3%) | 4 (4.8%)
Effective treatmentb | 40 (48.8%) | 9 (10.8%) | 44 (48.4%) | 9 (10.8%)
Mycological curec | 56 (68.3%) | 13 (15.7%) | 61 (67.0%) | 15 (18.1%)

a Mycological cure and an absence of clinical signs and symptoms (erythema, scaling, fissuring, maceration, vesiculation, or pruritus).
b Mycological cure and no or mild erythema and/or scaling with all other signs and symptoms absent.
c Negative KOH and fungal culture.

16 HOW SUPPLIED/ STORAGE AND HANDLING

Ecoza topical foam, 1% is white to off-white foam supplied in 10g (NDC 81811-100-10) and 70g (NDC 81811-100-70) aluminum pressurized canister.

STORAGE AND HANDLING

Store at controlled room temperature 20°C to 25°C (68°F to 77°F) with excursions permitted between 15°C and 30°C (59°F and 86°F). Do not refrigerate or freeze.

Ecoza topical foam is flammable. Avoid heat, flame, and smoking during and immediately following application.

Contents under pressure. Do not puncture and/or incinerate the containers.

Do not expose containers to heat and/or store at temperatures above 120°F (49°C) even when empty.

Do not store in direct sunlight.

17 PATIENT COUNSELING INFORMATION

See FDA-approved patient labeling (Patient Information)

The patient should be instructed as follows:

- Inform patients that Ecoza (econazole nitrate) topical foam, 1% is for topical use only. Ecoza (econazole nitrate) topical foam, 1% is not intended for oral, intravaginal, or ophthalmic use.
- Ecoza topical foam, 1% is flammable; avoid heat, flame, and smoking during and immediately following application.
- If a reaction suggesting sensitivity or chemical irritation develops with the use of Ecoza topical foam, 1%, use of the medication should be discontinued.

Manufactured in the USA for

Resilia Pharmaceuticals, Inc.
Atlanta, GA 30328

PRODERM TECHNOLOGY®

U.S, Patent 5,993,830

ECOPI-022-2023-001

Issued: 12/2023

P/N 141333

Patient Information
ECOZA® (ee-ko-zah)
(econazole nitrate) topical foam, 1%

Important information: Ecoza topical foam is for use on skin only. Do not use Ecoza topical foam in your eyes or vagina.

What is Ecoza topical foam?
Ecoza topical foam is a prescription medicine used on the skin (topical) to treat athlete's foot that is between the toes (interdigital tinea pedis) in people 12 years of age and older.

What should I tell my doctor before using Ecoza topical foam?
Before using Ecoza topical foam, tell your doctor about all of your medical conditions, including if you:

- are pregnant or plan to become pregnant. It is not known if Ecoza topical foam will harm your unborn baby.
- are breastfeeding or plan to breastfeed. It is not known if Ecoza topical foam passes into your breast milk.

Tell your doctor about all the medicines you take, including prescription and over-the-counter medicines, vitamins, and herbal supplements.

How should I use Ecoza topical foam?
See the detailed Instructions for Use for information about how to use Ecoza topical foam.

- Use Ecoza topical foam exactly as your doctor tells you to use it.
- Apply Ecoza topical foam to the affected skin areas of your feet 1 time a day for 4 weeks.
- If Ecoza topical foam gets in or near your eyes, rinse them well with water.
- Wash your hands after you apply Ecoza topical foam.

What should I avoid while using Ecoza topical foam?

- Ecoza topical foam is flammable. Avoid heat, flame and smoking while applying and right after you apply Ecoza topical foam to your skin.

What are the possible side effects of Ecoza topical foam?
Ecoza topical foam may cause skin reactions at the treatment site. Tell your doctor if you have any skin reactions on the areas of your skin treated with Ecoza topical foam.
These are not all the possible side effects of Ecoza topical foam.
Call your doctor for medical advice about side effects. You may report side effects to FDA at 1-800-FDA-1088.

How should I store Ecoza topical foam?

- Store Ecoza topical foam at room temperature, between 68°F to 77°F (20°C to 25°C).
- Do not refrigerate or freeze Ecoza topical foam.
- Do not store Ecoza topical foam in direct sunlight.
- Ecoza topical foam is flammable. Keep the Ecoza topical foam canister away from heat and temperatures above 120°F (49°C), even if the canister is empty.
- Do not puncture or burn the Ecoza topical foam canister.

Keep Ecoza topical foam and all medicines out of the reach of children.

General information about the safe and effective use of Ecoza topical foam
Medicines are sometimes prescribed for purposes other than those listed in a Patient Information leaflet. You can ask your doctor or pharmacist for information about Ecoza topical foam that is written for health professionals. Do not use Ecoza topical foam for a condition for which it was not prescribed. Do not give Ecoza topical foam to other people, even if they have the same symptoms that you have. It may harm them.

What are the ingredients in Ecoza topical foam?
Active ingredient: econazole nitrate USP
Inactive Ingredients: dimethicone, glycerin, polysorbate 20, povidone, propylene glycol, stearic acid, trolamine, purified water and butane as a propellant.
Manufactured for Resilia Pharmaceuticals, Inc., Atlanta, GA 30328
For more information call Resilia Pharmaceuticals, Inc., at 888-998-0770.

This Patient Information has been approved by the U.S. Food and Drug Administration.

Issued: 12/2023

P/N 141333 ECOPI-022-2023-001

Instructions for Use ECOZA®(ee-ko-zah) (econazole nitrate) topical foam, 1%

Important information: Ecoza topical foam is for use on skin only.

Do not use Ecoza topical foam in your eyes or vagina.

Parts of Ecoza topical foam Canister. (See Figure A)

Figure A

How to apply Ecoza topical foam:

Step 1: | Before you apply Ecoza topical foam, shake the Ecoza topical foam canister for about 5 seconds.
Step 2: | Remove the cap and turn the Ecoza topical foam canister upside down over the palm of your hand.
Step 3: | Press down firmly on the actuator until there is a small amount of foam about the size of a golf ball in the palm of your hand. (See Figures B and C)

Figure B

Figure C

Step 4: | Use your finger-tips to scoop up small amounts of Ecoza topical foam and apply to the affected skin areas on your feet. Gently rub the foam into the skin. (See Figure D)
Figure D
Step 5: | You should apply Ecoza topical foam to your toes, to the spaces between your toes, and to the surrounding areas 1 time a day for 4 weeks or as prescribed by your doctor.
Step 6: | Replace the cap. Wash your hands after applying Ecoza topical foam.

How should I store Ecoza topical foam?

- Store Ecoza topical foam at room temperature, between 68°F to 77°F (20°C to 25°C).
- Do not refrigerate or freeze Ecoza topical foam.
- Do not store Ecoza topical foam in direct sunlight.
- Ecoza topical foam is flammable. Keep the Ecoza topical foam canister away from heat and temperatures above 120°F (49°C), even if the canister is empty.
- Do not puncture or burn the Ecoza topical foam canister.

Keep Ecoza topical foam and all medicines out of the reach of children.

This Instructions for Use has been approved by the U.S. Food and Drug Administration.

Manufactured for Resilia Pharmaceuticals, Inc., Atlanta, GA 30328

Issued: 12/2023

PRINCIPAL DISPLAY PANEL - 70 g Canister Label

NDC 81811-100-70

ecoza™
(econazole nitrate)
topical foam, 1%

For Topical Use Only

Not for ophthalmic, oral or intravaginal use.

Keep Out of Reach of Children

Rx Only
Net Wt 70g

Resilia Pharmaceuticals, Inc.

PRINCIPAL DISPLAY PANEL - 70 g Canister Carton

NDC 81811-0100-70

ecoza™
(econazole nitrate)
topical foam, 1%

For Topical Use Only

Not for ophthalmic, oral or intravaginal use.

Keep Out of Reach of Children

Rx Only
Net Wt 70g

Resilia Pharmaceuticals, Inc.